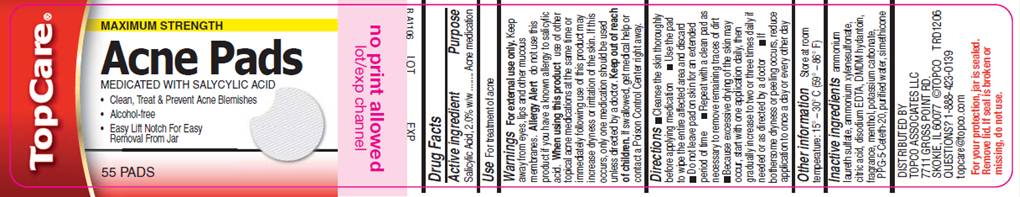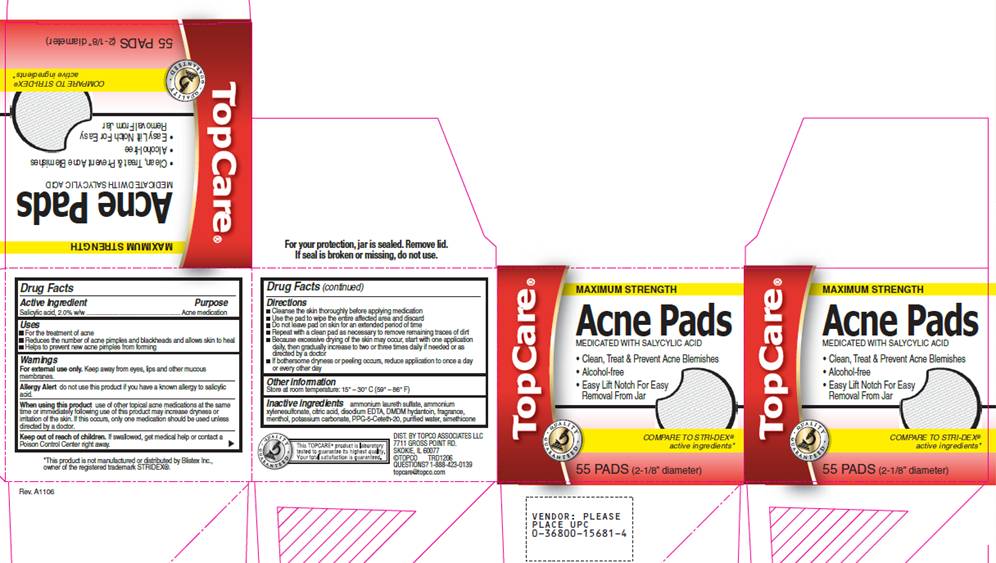 DRUG LABEL: Medicated Acne Pads
NDC: 50730-7701 | Form: SWAB
Manufacturer: H and P Industries, Inc. dba Triad Group
Category: otc | Type: HUMAN OTC DRUG LABEL
Date: 20091228

ACTIVE INGREDIENTS: SALICYLIC ACID .02 mL/1 1
INACTIVE INGREDIENTS: CITRIC ACID MONOHYDRATE; EDETATE DISODIUM; 1,3-DIMETHYLOL-5,5-DIMETHYL-HYDANTOIN; MENTHOL; POTASH; CETETH-20; WATER

DRUG FACTS

ACTIVE INGREDIENT

Salicylic acid 2.0% w/w

PURPOSE

Acne medication

USES

- for the treatment and management of acne
- reduces the number of acne pimples and blackheads and allows skin to heal
- helps to prevent new acne pimples from forming

WARNINGS

For external use only. Keep away from eyes, lips and other mucous membranes.

Allergy alert

do not use this product if you have a known allergy to salicylic acid.

When using this product

use of other topical acne medications at the same time or immediately following use of this product may increase dryness or irritation of the skin. If this occurs, only one medication should be used unless directed by a doctor.

Keep out of reach of children

If swallowed, get medical help or contact a Poison Control Center right away.

DIRECTIONS

- Cleanse the skin thoroughly before applying medication
- Use the pad to wipe the entire affected area and discard
- Do not leave pad on skin for an extended period of time
- Repeat with a clean pad as necessary to remove remaining traces of dirt
- Because excessive drying of the skin may occur, start with one application daily, then gradually increase to two or three times daily if needed or as directed by a doctor
- If bothersome dryness of peeling occurs, reduce application to once a day or every other day

OTHER INFORMATION

Store at room temperature: 15°- 30° C (59° - 86° F)

INACTIVE INGREDIENTS

ammonium laureth sulfate, ammonium xylenesulfonate, citric acid, disodium EDTA, DMDM hydantoin, fragrance, menthol, potassium carbonate, PPG-5-ceteth-20, purified water, simethicone

LABEL INFORMATION - REPRESENTATIVE LABEL

MAXIMUM STRENGTH

ACNE PADS

MEDICATED WITH SALYCYLIC ACID

- Clean, Treat and Prevent Acne Blemishes
- Alcohol-free
- Easy Lift Notch For Easy Removal From Jar

55 PADS

BOX INFORMATION - REPRESENTATIVE BOX

MAXIMUM STRENGTH
ACNE PADS
MEDICATED WITH SALYCYLIC ACID

- Clean, Treat and Prevent Acne Blemishes
- Alcohol-free
- Easy Lift Notch For Easy Removal From Jar

Compare to STRI-DEX® active ingredients*

55 PADS (2-1/8" diameter)

*This product is not manufactured or distributed by Blistex, Inc., owner of the registered trademark STRIDEX®.